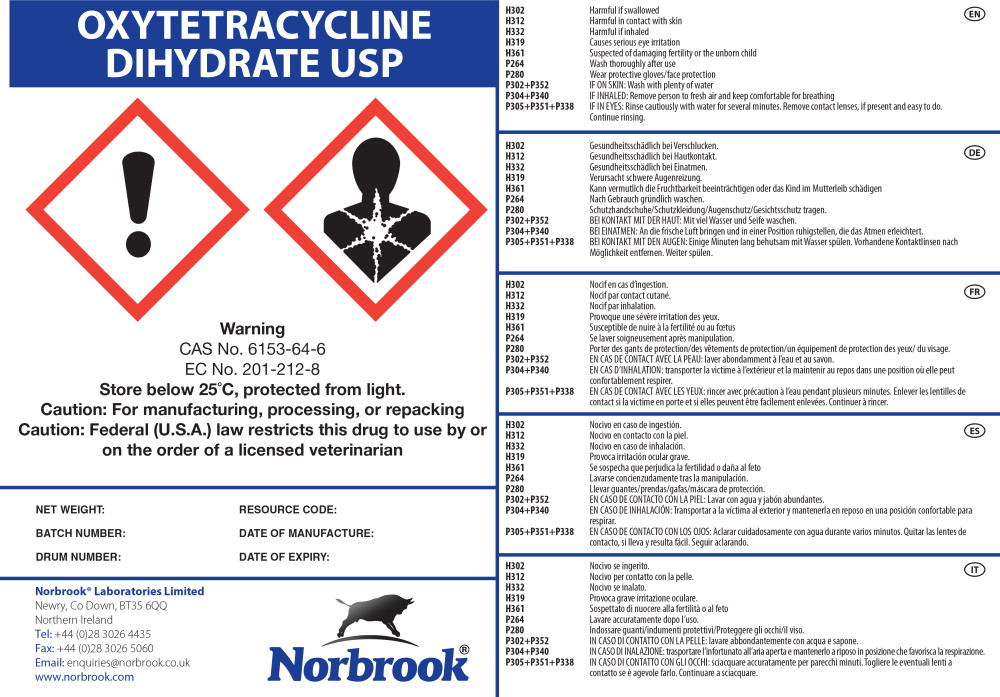 DRUG LABEL: Oxytetracycline Dihydrate
NDC: 55529-650 | Form: POWDER
Manufacturer: Norbrook Laboratories Limited
Category: other | Type: BULK INGREDIENT - ANIMAL DRUG
Date: 20170515

ACTIVE INGREDIENTS: Oxytetracycline 1 kg/1 kg

Principal Display Panel - Drum Label

OXYTETRACYCLINE

DIHYDRATE USP

Warning

CAS No. 6153-64-6

EC No. 201-212-8

Store below 25°C, protected from light.

Caution: For manufacturing, processing, or repacking
Caution: Federal (U.S.A.) law restricts this drug to use by or
on the order of a licensed veterinarian

NET WEIGHT: RESOURCE CODE:

BATCH NUMBER: DATE OF MANUFACTURE:

DRUM NUMBER: DATE OF EXPIRY:

Norbrook® Laboratories Limited

Newry, Co Down, BT35 6QQ

Northern Ireland

Tel: +44 (0)28 3026 4435

Fax: +44 (0)28 3026 5060

Email: enquiries@norbrook.co.uk

www.norbrook.com

Norbrook®